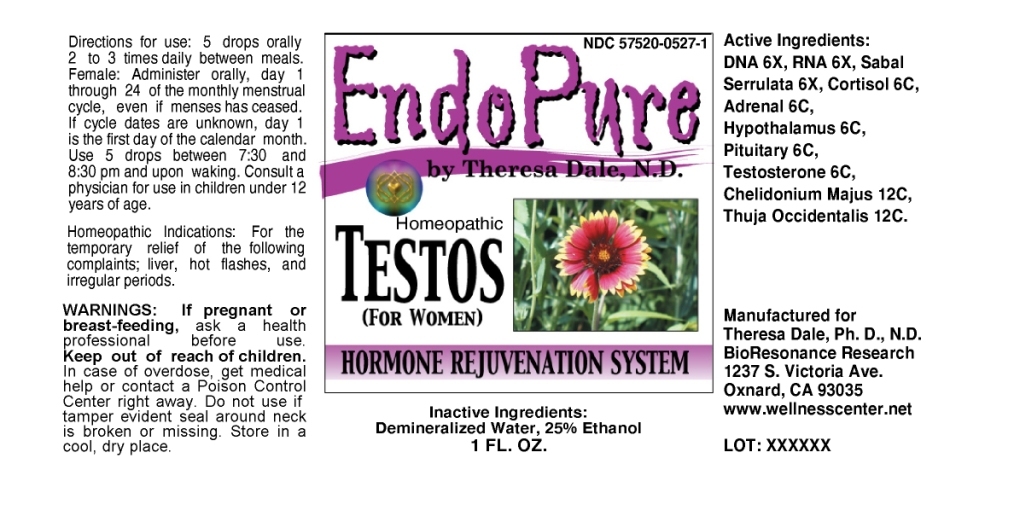 DRUG LABEL: Endo Pure Testos (for Women)
NDC: 57520-0527 | Form: LIQUID
Manufacturer: Apotheca Company
Category: homeopathic | Type: HUMAN OTC DRUG LABEL
Date: 20110628

ACTIVE INGREDIENTS: SAW PALMETTO 6 [hp_X]/1 mL; HYDROCORTISONE 6 [hp_C]/1 mL; SUS SCROFA ADRENAL GLAND 6 [hp_C]/1 mL; SUS SCROFA HYPOTHALAMUS 6 [hp_C]/1 mL; SUS SCROFA PITUITARY GLAND 6 [hp_C]/1 mL; TESTOSTERONE 6 [hp_C]/1 mL; CHELIDONIUM MAJUS 12 [hp_C]/1 mL; THUJA OCCIDENTALIS LEAFY TWIG 12 [hp_C]/1 mL; SACCHAROMYCES CEREVISIAE RNA 6 [hp_X]/1 mL; HERRING SPERM DNA 6 [hp_X]/1 mL
INACTIVE INGREDIENTS: WATER; ALCOHOL

Endo Pure Testos (for Women)

ACTIVE INGREDIENT

ACTIVE INGREDIENTS: DNA 6X, RNA 6X, Sabal serrulata 6X, Cortisol (hydrocortisone) 6C, Glandula suprarenalis 6C, Hypothalamus 6C, Pituitary 6C, Testosterone 6C, Chelidonium majus 12C, Thuja occidentalis 12C.

PURPOSE

HOMEOPATHIC INDICATIONS: For the temporary relief of the following complaints; liver, hot flashes, and irregular periods.

WARNINGS

WARNINGS: If pregnant or breast-feeding, ask a health professional before use.

Keep out of reach of children. In case of overdose, get medical help or contact a Poison Control Center right away.

Do not use if tamper evident seal around neck is broken or missing. Store in a cool, dry place.

DOSAGE AND ADMINISTRATION

DIRECTONS FOR USE: 5 drops orally 2 to 3 times daily between meals. Female: Administer orally, day 1 through 24 of the monthly menstrual cycle, even is menses has ceased. If cycle dates are unknown, day 1 is the first day of the calendar month. Use 5 drops between 7:30 and 8:30 pm and upon waking. Consult a physician for use in children under 12 years of age.

INACTIVE INGREDIENTS: Demineralized water, 25% Ethanol.

KEEP OUT OF REACH OF CHILDREN. In case of overdose, get medical help or contact a Poison Control Center right away.

INDICATIONS AND USAGE

HOMEOPATHIC INDICATIONS: For the temporary relief of the following complaints; liver, hot flashes, and irregular periods.

QUESTIONS

Manufactured for

Theresa Dale, Ph. D., N.D.

BioResonance Research

1237 S. Victoria Ave.

Oxnard, CA 93035

www.wellnesscenter.net

PACKAGE LABEL

NDC 57520-0527-1

Endo Pure Testos (for Women)

Homeopathic

HORMONE REJUVENATION SYSTEM

1 FL. OZ